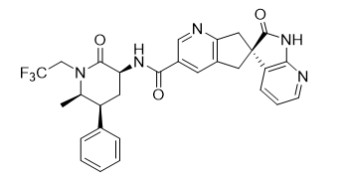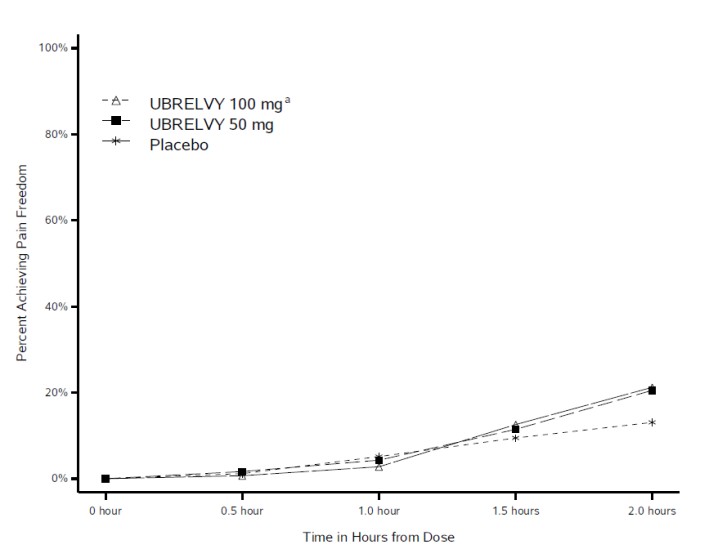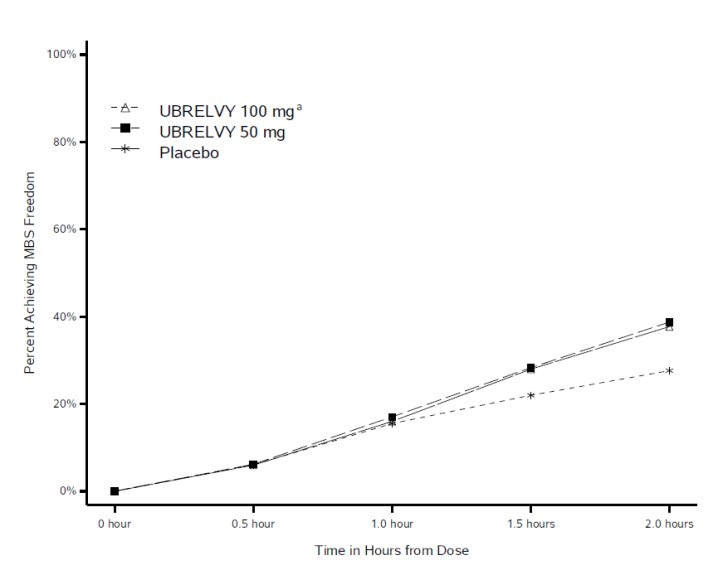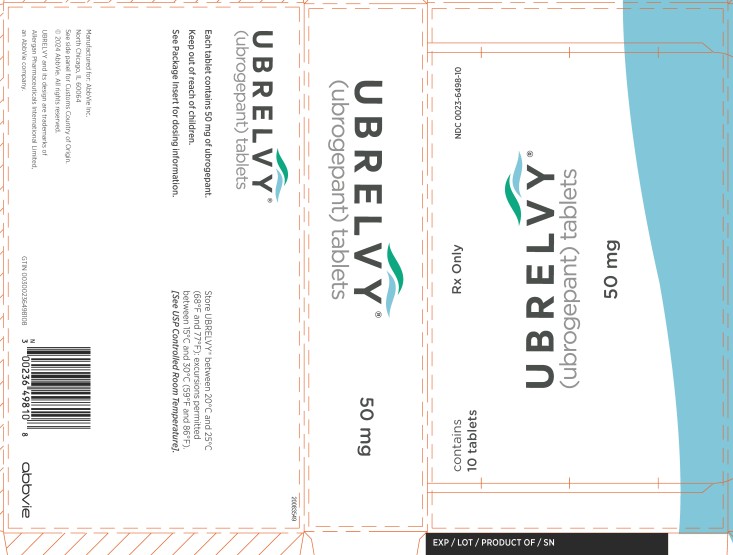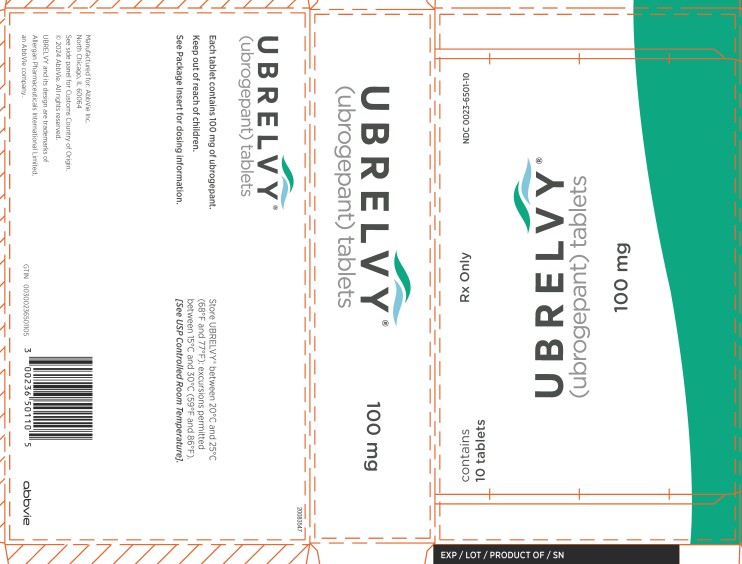 DRUG LABEL: UBRELVY
NDC: 0023-6498 | Form: TABLET
Manufacturer: Allergan, Inc.
Category: prescription | Type: HUMAN PRESCRIPTION DRUG LABEL
Date: 20250605

ACTIVE INGREDIENTS: UBROGEPANT 50 mg/1 1
INACTIVE INGREDIENTS: VITAMIN E POLYETHYLENE GLYCOL SUCCINATE; MANNITOL; MICROCRYSTALLINE CELLULOSE; SODIUM CHLORIDE; CROSCARMELLOSE SODIUM; SODIUM STEARYL FUMARATE; SILICON DIOXIDE; COPOVIDONE K25-31

HIGHLIGHTS OF PRESCRIBING INFORMATION

These highlights do not include all the information needed to use UBRELVY safely and effectively. See full prescribing information for UBRELVY.
UBRELVY® (ubrogepant) tablets, for oral use
Initial U.S. Approval: 2019

RECENT MAJOR CHANGES

Warnings and Precautions (5.2, 5.3) | 3/2025

1 INDICATIONS AND USAGE

UBRELVY is a calcitonin gene-related peptide receptor antagonist indicated for the acute treatment of migraine with or without aura in adults. (1)

Limitations of Use

UBRELVY is not indicated for the preventive treatment of migraine. (1)

2 DOSAGE AND ADMINISTRATION

- The recommended dose is 50 mg or 100 mg taken orally, as needed. (2.1)
- If needed, a second dose may be administered at least 2 hours after the initial dose. (2.1)
- The maximum dose in a 24-hour period is 200 mg. (2.1)
- Severe Hepatic or Severe Renal Impairment: Recommended dose is 50 mg; if needed, a second 50 mg dose may be taken at least 2 hours after the initial dose. (2.2, 8.6, 8.7)

3 DOSAGE FORMS AND STRENGTHS

Tablets: 50 mg and 100 mg (3)

4 CONTRAINDICATIONS

- Concomitant use with strong CYP3A4 inhibitors. (4)
- History of serious hypersensitivity to ubrogepant or any component of UBRELVY. (4)

5 WARNINGS AND PRECAUTIONS

- Hypersensitivity Reactions: If a serious hypersensitivity reaction occurs, discontinue UBRELVY and initiate appropriate therapy. Severe hypersensitivity reactions have included anaphylaxis and dyspnea. These reactions can occur within minutes, hours, or days after administration. (5.1)
- Hypertension: New-onset or worsening of pre-existing hypertension may occur. (5.2)
- Raynaud’s phenomenon: New-onset or worsening of pre-existing Raynaud’s phenomenon may occur. (5.3)

6 ADVERSE REACTIONS

The most common adverse reactions (at least 2% and greater than placebo) were nausea and somnolence. (6.1)

To report SUSPECTED ADVERSE REACTIONS, contact AbbVie at 1-800-678-1605 or FDA at 1-800-FDA-1088 or www.fda.gov/medwatch.

7 DRUG INTERACTIONS

- Strong CYP3A4 Inducers: Should be avoided as concomitant use will result in reduction of ubrogepant exposure. (2.2, 7.2)
- For additional dose modifications for moderate or weak CYP3A4 inhibitors and inducers or BCRP and/or P-gp only inhibitors, refer to section 2.2. (7.1, 7.2, 7.3)

8 USE IN SPECIFIC POPULATIONS

- Pregnancy: Based on animal data, may cause fetal harm. (8.1)
- Avoid use in patients with end-stage renal disease. (8.7)

FULL PRESCRIBING INFORMATION

1 INDICATIONS AND USAGE

UBRELVY is indicated for the acute treatment of migraine with or without aura in adults.

Limitations of Use

UBRELVY is not indicated for the preventive treatment of migraine.

2 DOSAGE AND ADMINISTRATION

2.1 Recommended Dosage

The recommended dose of UBRELVY is 50 mg or 100 mg taken orally with or without food.

If needed, a second dose may be taken at least 2 hours after the initial dose. The maximum dose in a 24-hour period is 200 mg. The safety of treating more than 8 migraines in a 30-day period has not been established.

2.2 Dosage Modifications

Dosing modifications for concomitant use of specific drugs and for patients with hepatic or renal impairment are provided in Table 1.

Table 1: Dose Modifications for Drug Interactions and for Specific Populations
Dosage Modifications | Initial Dose | Second Dosea (if needed)
Concomitant Drug [see Drug Interactions (7)]
Moderate CYP3A4 Inhibitors (7.1) | 50 mg | Avoid within 24 hours
Weak CYP3A4 Inhibitors (7.1) | 50 mg | 50 mg
Strong CYP3A4 Inducers (7.2) | Avoid concomitant use
Weak & Moderate CYP3A4 Inducers (7.2) | 100 mg | 100 mg
BCRP and/or P-gp only Inhibitors (7.3) | 50 mg | 50 mg
Specific Populations [see Use in Specific Populations (8)]
Severe Hepatic Impairment (Child-Pugh Class C) (8.6) | 50 mg | 50 mg
Severe Renal Impairment (CLcr 15-29 mL/min) (8.7) | 50 mg | 50 mg
End-Stage Renal Disease (CLcr <15 mL/min) (8.7) | Avoid use
a Second dose may be taken at least 2 hours after the initial dose

3 DOSAGE FORMS AND STRENGTHS

UBRELVY 50 mg is supplied as white to off-white, capsule-shaped, biconvex tablets debossed with “U50” on one side.

UBRELVY 100 mg is supplied as white to off-white, capsule-shaped, biconvex tablets debossed with “U100” on one side.

4 CONTRAINDICATIONS

UBRELVY is contraindicated:

- With concomitant use of strong CYP3A4 inhibitors [see Drug Interactions (7.1)]
- In patients with a history of serious hypersensitivity to ubrogepant or any component of UBRELVY. Reactions have included anaphylaxis, dyspnea, and facial or throat edema [see Warnings and Precautions (5.1)]

5 WARNINGS AND PRECAUTIONS

5.1 Hypersensitivity Reactions

Hypersensitivity reactions, including anaphylaxis, dyspnea, facial or throat edema, rash, urticaria, and pruritus, have been reported with use of UBRELVY. Hypersensitivity reactions can occur minutes, hours, or days after administration. Most reactions occurred within hours after dosing and were not serious, and some reactions led to discontinuation. If a serious or severe hypersensitivity reaction occurs, discontinue UBRELVY and institute appropriate therapy [see Contraindications (4) and Adverse Reactions (6.2)].

5.2 Hypertension

Development of hypertension and worsening of pre-existing hypertension have been reported following the use of CGRP antagonists, including UBRELVY, in the postmarketing setting. Some of the patients who developed new-onset hypertension had risk factors for hypertension. There were cases requiring initiation of pharmacological treatment for hypertension and, in some cases, hospitalization. Hypertension may occur at any time during treatment, but was most frequently reported within 7 days of therapy initiation. The CGRP antagonist was discontinued in many of the reported cases.

Monitor patients treated with UBRELVY for new-onset hypertension, or worsening of pre-existing hypertension, and consider whether discontinuation of UBRELVY is warranted if evaluation fails to establish an alternative etiology or blood pressure is inadequately controlled.

5.3 Raynaud’s Phenomenon

Development of Raynaud’s phenomenon and recurrence or worsening of pre-existing Raynaud’s phenomenon have been reported in the postmarketing setting following the use of CGRP antagonists, including UBRELVY. In reported cases with small molecule CGRP antagonists, symptom onset occurred a median of 1.5 days following dosing. Many of the cases reported serious outcomes, including hospitalizations and disability, generally related to debilitating pain. In most reported cases, discontinuation of the CGRP antagonist resulted in resolution of symptoms.

UBRELVY should be discontinued if signs or symptoms of Raynaud’s phenomenon develop, and patients should be evaluated by a healthcare provider if symptoms do not resolve. Patients with a history of Raynaud’s phenomenon should be monitored for, and informed about the possibility of, worsening or recurrence of signs and symptoms.

6 ADVERSE REACTIONS

The following clinically significant adverse reactions are described elsewhere in labeling:

- Hypersensitivity Reactions [see Warnings and Precautions (5.1)]
- Hypertension [see Warnings and Precautions (5.2)]
- Raynaud’s Phenomenon [see Warnings and Precautions (5.3)]

6.1 Clinical Trials Experience

Because clinical trials are conducted under widely varying conditions, adverse reaction rates observed in the clinical trials of a drug cannot be directly compared to rates in the clinical trials of another drug and may not reflect the rates observed in practice.

The safety of UBRELVY was evaluated in 3,624 subjects who received at least one dose of UBRELVY. In two randomized, double-blind, placebo-controlled, Phase 3 trials in adult patients with migraine (Studies 1 and 2), a total of 1,439 patients received UBRELVY 50 mg or 100 mg [see Clinical Studies (14)]. Of the UBRELVY-treated patients in these 2 studies, approximately 89% were female, 82% were White, 15% were Black, and 17% were of Hispanic or Latino ethnicity. The mean age at study entry was 41 years (range of 18-75 years).

Long-term safety was assessed in 813 patients, dosing intermittently for up to 1 year in an open-label extension study. Patients were permitted to treat up to 8 migraines per month with UBRELVY. Of these 813 patients, 421 patients were exposed to 50 mg or 100 mg for at least 6 months, and 364 patients were exposed to these doses for at least one year, all of whom treated at least two migraine attacks per month, on average. In that study, 2.5% of patients were withdrawn from UBRELVY because of an adverse reaction. The most common adverse reaction resulting in discontinuation in the long-term safety study was nausea.

Adverse reactions in Studies 1 and 2 are shown in Table 2.

Table 2: Adverse Reactions Occurring in At Least 2% and at a Frequency Greater than Placebo in Studies 1 and 2
 | Placebo (N= 984) % | UBRELVY 50 mg (N=954) % | UBRELVY 100 mg (N=485) %
Nausea | 2 | 2 | 4
Somnolence* | 1 | 2 | 3
Dry Mouth | 1 | <1 | 2

*Somnolence includes the adverse reaction-related terms sedation and fatigue.

6.2 Postmarketing Experience

The following adverse reactions have been identified during post-approval use of UBRELVY. Because these reactions are reported voluntarily from a population of uncertain size, it is not always possible to reliably estimate their frequency or establish a causal relationship to drug exposure.

Immune System Disorders: Hypersensitivity (e.g., anaphylaxis, dyspnea, facial or throat edema, rash, urticaria, and pruritus) [see Contraindications (4) and Warnings and Precautions (5.1)]

Vascular Disorders: Hypertension [see Warnings and Precautions (5.2)], Raynaud’s phenomenon [see Warnings and Precautions (5.3)]

7 DRUG INTERACTIONS

7.1 CYP3A4 Inhibitors

Co-administration of UBRELVY with ketoconazole, a strong CYP3A4 inhibitor, resulted in a significant increase in exposure of ubrogepant [see Clinical Pharmacology (12.3)]. UBRELVY should not be used with strong CYP3A4 inhibitors (e.g., ketoconazole, itraconazole, clarithromycin) [see Contraindications (4)].

Co-administration of UBRELVY with verapamil, a moderate CYP3A4 inhibitor, resulted in an increase in ubrogepant exposure [see Clinical Pharmacology (12.3)]. Dose adjustment is recommended with concomitant use of UBRELVY and moderate CYP3A4 inhibitors (e.g., cyclosporine, ciprofloxacin, fluconazole, fluvoxamine, grapefruit juice) [see Dosage and Administration (2.2)].

No dedicated drug interaction study was conducted with ubrogepant and weak CYP3A4 inhibitors. Dose adjustment is recommended with concomitant use of UBRELVY with weak CYP3A4 inhibitors [see Dosage and Administration (2.2)].

7.2 CYP3A4 Inducers

Co-administration of UBRELVY with rifampin, a strong CYP3A4 inducer, resulted in a significant reduction in ubrogepant exposure [see Clinical Pharmacology (12.3)]. In patients taking strong CYP3A4 inducers (e.g., phenytoin, barbiturates, rifampin, St. John’s Wort), loss of ubrogepant efficacy is expected, and concomitant use should be avoided.

Co-administration of UBRELVY with moderate or weak CYP3A4 inducers was not evaluated in a clinical study. Dose adjustment is recommended with concomitant use of UBRELVY and moderate or weak CYP3A4 inducers [see Dosage and Administration (2.2)].

7.3 BCRP and/or P-gp Only Inhibitors

Ubrogepant is a substrate of BCRP and P-gp efflux transporters. Use of BCRP and/or P-gp only inhibitors (e.g., quinidine, carvedilol, eltrombopag, curcumin) may increase the exposure of ubrogepant [see Clinical Pharmacology (12.3)]. Clinical drug interaction studies with inhibitors of these transporters were not conducted. Dose adjustment is recommended with BCRP and/or P-gp only inhibitors [see Dosage and Administration (2.2)].

8 USE IN SPECIFIC POPULATIONS

8.1 Pregnancy

Pregnancy Exposure Registry

There is a pregnancy exposure registry that monitors outcomes in women who become pregnant while taking UBRELVY. Patients should be encouraged to enroll by calling 1-833-277-0206 or visiting http://empresspregnancyregistry.com.

Risk Summary

There are no adequate data on the developmental risk associated with the use of UBRELVY in pregnant women. In animal studies, adverse effects on embryofetal development were observed following administration of ubrogepant during pregnancy (increased embryofetal mortality in rabbits) or during pregnancy and lactation (decreased body weight in offspring in rats) at doses greater than those used clinically and which were associated with maternal toxicity (see Data).

In the U.S. general population, the estimated background risk of major birth defects and miscarriages in clinically recognized pregnancies is 2-4% and 15-20%, respectively. The estimated rate of major birth defects (2.2% -2.9%) and miscarriage (17%) among deliveries to women with migraine are similar to rates reported in women without migraine.

Clinical Considerations

Disease-Associated Maternal and/or Embryo/Fetal Risk

Published data have suggested that women with migraine may be at increased risk of preeclampsia and gestational hypertension during pregnancy.

Data

Animal Data

Oral administration of ubrogepant (0, 1.5, 5, 25, 125 mg/kg/day) to pregnant rats during the period of organogenesis resulted in no adverse effects on embryofetal development. Plasma exposure (AUC) at the highest dose tested is approximately 45 times that in humans at the maximum recommended human dose (MRHD) of 200 mg/day.

In pregnant rabbits, ubrogepant (0, 15, 45, 75, or 250 mg/kg/day) was administered orally throughout organogenesis in two separate studies. In both studies, the highest dose tested (250 mg/kg/day) was associated with maternal toxicity. In the first study, ubrogepant produced abortion and increased embryofetal mortality in surviving litters at the high dose (250 mg/kg/day). In the second study, excessive maternal toxicity at the high dose (250 mg/kg/day) resulted in early termination and lack of fetal data for that dose group. Plasma exposure (AUC) at the highest no-effect dose (75 mg/kg/day) for adverse effects on embryofetal development in rabbit is approximately 8 times that in humans at the MRHD.

Oral administration of ubrogepant (0, 25, 60, or 160 mg/kg/day) to rats throughout gestation and lactation resulted in decreased body weight in offspring at birth and during the lactation period at the mid and high doses, which were associated with maternal toxicity. Plasma exposure (AUC) at the no-effect dose for adverse effects on pre- and postnatal development in rats (25 mg/kg/day) is approximately 15 times that in humans at the MRHD.

8.2 Lactation

Risk Summary

Data from a lactation study in twelve healthy adult females indicate that ubrogepant is excreted in breast milk in low amounts. The estimated relative infant dose is approximately 0.15% of the maternal weight-adjusted dose, and the milk-to-plasma ratio is 0.23 (see Data). There are no data on the effects of ubrogepant on the breastfed infant or the effects on milk production. The developmental and health benefits of breastfeeding should be considered along with the mother’s clinical need for UBRELVY and any potential adverse effects on the breastfed infant from UBRELVY or from the underlying maternal condition.

Data

A study was conducted in twelve healthy adult lactating females who were between 24 and 34 years of age and between 1 month and 6 months postpartum. Each subject was administered a single oral dose of ubrogepant 100 mg. Maternal plasma and breast milk were collected for 24 hours after dosing. Using a 150 mL/kg/day estimated infant milk intake, the mean estimated relative infant dose was approximately 0.15% of the maternal weight-adjusted dose. The mean milk-to-plasma ratio was 0.23. All subjects had detectable levels of ubrogepant in breast milk during the study; by 16 to 24 hours after dosing, 17% of females in the study had detectable levels of ubrogepant in breast milk. The mean cumulative amount of ubrogepant excreted in breast milk over 24 hours was less than 0.02 mg of a 100 mg dose.

8.4 Pediatric Use

Safety and effectiveness in pediatric patients have not been established.

8.5 Geriatric Use

In pharmacokinetic studies, no clinically significant pharmacokinetic differences were observed between elderly and younger subjects. Clinical studies of UBRELVY did not include sufficient numbers of patients aged 65 years and over to determine whether they respond differently from younger patients. In general, dose selection for an elderly patient should be cautious, usually starting at the low end of the dosing range.

8.6 Hepatic Impairment

In patients with pre-existing mild (Child-Pugh Class A), moderate (Child-Pugh Class B), or severe hepatic impairment (Child-Pugh Class C), ubrogepant exposure was increased by 7%, 50%, and 115%, respectively. No dose adjustment is recommended for patients with mild or moderate hepatic impairment. Dose adjustment for UBRELVY is recommended for patients with severe hepatic impairment [see Dosage and Administration (2.2)].

8.7 Renal Impairment

The renal route of elimination plays a minor role in the clearance of ubrogepant [see Clinical Pharmacology (12.3)]. No dose adjustment is recommended for patients with mild or moderate renal impairment. Dose adjustment is recommended for patients with severe renal impairment (CLcr 15-29 mL/min) [see Dosage and Administration (2.2) and Clinical Pharmacology (12.3)]. Avoid use of UBRELVY in patients with end-stage renal disease (ESRD) (CLcr <15 mL/min).

10 OVERDOSAGE

The elimination half-life of ubrogepant is approximately 5 to 7 hours; therefore, monitoring of patients after overdose with UBRELVY should continue for at least 24 hours, or while symptoms or signs persist.

11 DESCRIPTION

The active ingredient of UBRELVY is ubrogepant, a calcitonin gene-related peptide (CGRP) receptor antagonist. The chemical name of ubrogepant is (3'S)-N-((3S,5S,6R)-6-methyl-2-oxo-5-phenyl-1-(2,2,2-trifluoroethyl)piperidin-3-yl)-2'-oxo-1',2',5,7-tetrahydrospiro[cyclopenta[b]pyridine-6,3'-pyrrolo[2,3-b]pyridine]-3-carboxamide and has the following structural formula:

The molecular formula is C29H26F3N5O3 and molecular weight is 549.6. Ubrogepant is a white to off-white powder. It is freely soluble in ethanol, methanol, acetone, and acetonitrile; and is practically insoluble in water.

UBRELVY is available as tablets for oral administration containing 50 mg or 100 mg ubrogepant. The inactive ingredients include colloidal silicon dioxide, croscarmellose sodium, mannitol, microcrystalline cellulose, polyvinylpyrrolidone vinyl acetate copolymer, sodium chloride, sodium stearyl fumarate, and vitamin E polyethylene glycol succinate.

12 CLINICAL PHARMACOLOGY

12.1 Mechanism of Action

Ubrogepant is a calcitonin gene-related peptide receptor antagonist.

12.2 Pharmacodynamics

Cardiac Electrophysiology

At a dose 2 times the maximum recommended daily dose, UBRELVY does not prolong the QT interval to any clinically relevant extent.

12.3 Pharmacokinetics

Absorption

Following oral administration of UBRELVY, ubrogepant is absorbed with peak plasma concentrations at approximately 1.5 hours. Ubrogepant displays dose-proportional pharmacokinetics within the recommended dose range [see Dosage and Administration (2.1)].

Effect of Food

When UBRELVY was administered with a high-fat meal, the time to maximum ubrogepant plasma concentration was delayed by 2 hours and resulted in a 22% reduction in Cmax with no change in AUC. UBRELVY was administered without regard to food in clinical efficacy studies [see Dosage and Administration (2.1)].

Distribution

Plasma protein binding of ubrogepant is 87% in vitro. The mean apparent central volume of distribution of ubrogepant (V/F) after single dose oral administration is approximately 350 L.

Elimination

Metabolism

Ubrogepant is eliminated mainly through metabolism, primarily by CYP3A4. The parent compound (ubrogepant), and 2 glucuronide conjugate metabolites were the most prevalent circulating components in human plasma. The glucuronide metabolites are not expected to contribute to the pharmacological activity of ubrogepant since they were reported as about 6000-fold less potent in the CGRP receptor binding assay.

Excretion

The elimination half-life of ubrogepant is approximately 5-7 hours. The mean apparent oral clearance (CL/F) of ubrogepant is approximately 87 L/hr. Ubrogepant is excreted mostly via the biliary/fecal route, while the renal route is a minor route of elimination. Following single oral dose administration of [^14C]-ubrogepant to healthy male subjects, 42% and 6% of the dose was recovered as unchanged ubrogepant in feces and urine, respectively.

Specific Populations

Patients with Renal Impairment

Population pharmacokinetic analysis based on pooled data from clinical studies was used to evaluate the effect of renal impairment characterized based on estimated creatinine clearance (CLcr) using the Cockcroft-Gault (C-G) equation. Renal impairment did not reveal a significant difference in the pharmacokinetics of ubrogepant in patients with mild or moderate renal impairment (CLcr 30-89 mL/min) relative to those with normal renal function (CLcr >90 mL/min). Patients with severe renal impairment or ESRD (eGFR <30 mL/min) have not been studied. Dose adjustment in patients with severe renal impairment (CLcr 15-29 mL/min) is recommended based on ADME information and a conservative assumption that severe renal impairment is unlikely to cause more than a two-fold increase in exposure of ubrogepant [see Dosage and Administration (2.2)]. No dosing recommendations can be made for patients with ESRD (CLcr<15 mL/min).

Patients with Hepatic Impairment

In patients with pre-existing mild (Child-Pugh Class A), moderate (Child-Pugh Class B), or severe hepatic impairment (Child-Pugh Class C), ubrogepant exposure was increased by 7%, 50%, and 115%, respectively. Patients with severe hepatic impairment require dose adjustments [see Dosage and Administration (2.2)].

Other Specific Populations

Based on a population pharmacokinetic analysis, age, sex, race, and body weight did not have a significant effect on the pharmacokinetics (Cmax and AUC) of ubrogepant. Therefore, no dose adjustments are warranted based on these factors.

Drug Interactions

In Vitro Studies

Enzymes

Ubrogepant is not an inhibitor of CYP1A2, 2B6, or 3A4. Ubrogepant is a weak inhibitor of CYP2C8, 2C9, 2D6, 2C19, MAO-A, and UGT1A1. The in vitro inhibition potential is not expected to be clinically significant. Ubrogepant is not an inducer of CYP1A2, 2B6, or 3A4 at clinically relevant concentrations.

Transporters

Ubrogepant is a substrate of BCRP and P-gp transporters in-vitro; therefore, use of inhibitors of BCRP and/or P-gp may increase the exposure of ubrogepant. Dose adjustment for concomitant use of UBRELVY with inhibitors of BCRP and/or P-gp is recommended based on ADME and clinical interaction studies with CYP3A4/P-gp inhibitors that show the highest predicted potential increase in exposure of ubrogepant is not expected to be more than two-fold [see Dosage and Administration (2.2) and Drug Interactions (7.3)].

Ubrogepant is a weak substrate of OATP1B1, OATP1B3, and OAT1, but not a substrate of OAT3. It is not an inhibitor of P-gp, BCRP, BSEP, MRP3, MRP4, OAT1, OAT3, or NTCP transporters, but is a weak inhibitor of OATP1B1, OATP1B3, and OCT2 transporters. Dose adjustments are needed only for P-gp, or BCRP inhibitors. No clinical drug interactions are expected for UBRELVY with other transporters.

In Vivo Studies

CYP3A4 Inhibitors [see Dosage and Administration (2.2), Contraindications (4), and Drug Interactions (7.1)]:

Co-administration of UBRELVY with ketoconazole, a strong CYP3A4 inhibitor, resulted in a 9.7-fold and 5.3-fold increase in AUCinf and Cmax of ubrogepant, respectively. Co-administration of UBRELVY with verapamil, a moderate CYP3A4 inhibitor, resulted in about 3.5-fold and 2.8-fold increase in AUCinf and Cmax of ubrogepant, respectively. No dedicated drug interaction study was conducted to assess concomitant use with weak CYP3A4 inhibitors. The conservative prediction of the maximal potential increase in ubrogepant exposure with weak CYP3A4 inhibitors is not expected to be more than 2-fold.

CYP3A4 Inducers [see Dosage and Administration (2.2) and Drug Interactions (7.2)]:

Co-administration of UBRELVY with rifampin, a strong CYP3A4 inducer, resulted in an 80% reduction in ubrogepant exposure. No dedicated drug interaction studies were conducted to assess concomitant use with weak or moderate CYP3A4 inducers. Dose adjustment for concomitant use of UBRELVY with weak or moderate CYP3A4 inducers is recommended based on a conservative prediction of 50% reduction in exposure of ubrogepant.

Other Drug-Drug Interaction Evaluations:

No significant pharmacokinetic interactions were observed for either ubrogepant or co-administered drugs when UBRELVY was administered with oral contraceptives (containing norgestimate and ethinyl estradiol), acetaminophen, naproxen, sumatriptan, esomeprazole, erenumab, galcanezumab, or atogepant.

13 NONCLINICAL TOXICOLOGY

13.1 Carcinogenesis, Mutagenesis, Impairment of Fertility

Carcinogenicity

Two-year oral carcinogenicity studies of ubrogepant were conducted in mice (0, 5, 15, or 50 mg/kg/day) and rats (0, 10, 30, or 100 mg/kg in males; 0, 10, 30, or 150 mg/kg in females). There was no evidence of drug-related tumors in either species. The highest dose tested in mice is similar to the maximum recommended human dose (200 mg/day) on a body surface area (mg/m^2) basis. Plasma exposure (AUC) at the highest dose tested in rats is approximately 25 times that in humans at the maximum recommended human dose (MRHD) of 200 mg/day.

Mutagenicity

Ubrogepant was negative in in vitro (Ames, chromosomal aberration test in Chinese Hamster Ovary cells) and in vivo (rat bone marrow micronucleus) assays.

Impairment of Fertility

Oral administration of ubrogepant (0, 20, 80, or 160 mg/kg/day) to male and female rats (mated with drug-naïve females and males, respectively) resulted in no adverse effects on fertility or reproductive performance. Plasma exposures (AUC) at the highest dose tested are approximately 30 times that in humans at the MRHD.

14 CLINICAL STUDIES

The efficacy of UBRELVY for the acute treatment of migraine was demonstrated in two randomized, double-blind, placebo-controlled trials [Study 1 (NCT02828020) and Study 2 (NCT02867709)]. Study 1 randomized patients to placebo (n=559) or UBRELVY 50 mg (n=556) or 100 mg (n=557) and Study 2 randomized patients to placebo (n=563) or UBRELVY 50 mg (n=562). In all studies, patients were instructed to treat a migraine with moderate to severe headache pain intensity. A second dose of study medication (UBRELVY or placebo), or the patient’s usual acute treatment for migraine, was allowed between 2 to 48 hours after the initial treatment for a non-responding or recurrent migraine headache. Up to 23% of patients were taking preventive medications for migraine at baseline. None of these patients were on concomitant preventive medication that act on the CGRP pathway.

The primary efficacy analyses were conducted in patients who treated a migraine with moderate to severe pain. The efficacy of UBRELVY was established by an effect on pain freedom at 2 hours post-dose and most bothersome symptom (MBS) freedom at 2 hours post-dose, compared to placebo, for Studies 1 and 2. Pain freedom was defined as a reduction of moderate or severe headache pain to no pain, and MBS freedom was defined as the absence of the self-identified MBS (i.e., photophobia, phonophobia, or nausea). Among patients who selected an MBS, the most commonly selected was photophobia (56%), followed by phonophobia (24%), and nausea (19%).

In both studies, the percentage of patients achieving headache pain freedom and MBS freedom 2 hours post-dose was significantly greater among patients receiving UBRELVY compared to those receiving placebo (see Table 3). Table 3 also presents the results of the analyses of the percentage of patients achieving pain relief at 2 hours (defined as a reduction in migraine pain from moderate or severe to mild or none) post-dose and the percentage of patients achieving sustained pain freedom between 2 to 24 hours post-dose.

The incidence of photophobia and phonophobia was reduced following administration of UBRELVY at both doses (50 mg and 100 mg) as compared to placebo.

Table 3: Migraine Efficacy Endpoints for Study 1 and Study 2
 | Study 1 |  |  | Study 2
 | UBRELVY 50 mg | UBRELVY 100 mg | Placebo | UBRELVY 50 mg | Placebo
Pain Free at 2 hours
N | 422 | 448 | 456 | 464 | 456
% Responders | 19.2 | 21.2 | 11.8 | 21.8 | 14.3
Difference from placebo (%) | 7.4 | 9.4 |  | 7.5
p value | 0.002 | <0.001 |  | 0.007
Most Bothersome Symptom Free at 2 hours
N | 420 | 448 | 454 | 463 | 456
% Responders | 38.6 | 37.7 | 27.8 | 38.9 | 27.4
Difference from placebo (%) | 10.8 | 9.9 |  | 11.5
p value | <0.001 | <0.001 |  | <0.001
Pain Relief at 2 hours
N | 422 | 448 | 456 | 464 | 456
% Responders | 60.7 | 61.4 | 49.1 | 62.7 | 48.2
p value | <0.001 | <0.001 |  | <0.001
Sustained Pain Freedom 2-24 hours
N | 418 | 441 | 452 | 457 | 451
% Responders | 12.7 | 15.4 | 8.6 | 14.4 | 8.2
p value | *NS | 0.002 |  | 0.005

* Not statistically significant (NS)

Figure 1 presents the percentage of patients achieving migraine pain freedom within 2 hours following treatment in Studies 1 and 2.

Figure 1: Percentage of Patients Achieving Pain Freedom within 2 Hours in Pooled Studies 1 and 2

a The 100 mg arm was only included in Study 1.

Figure 2 presents the percentage of patients achieving MBS freedom within 2 hours in Studies 1 and 2.

Figure 2: Percentage of Patients Achieving MBS Freedom within 2 Hours in Pooled Studies 1 and 2

a The 100 mg arm was only included in Study 1.

16 HOW SUPPLIED/STORAGE AND HANDLING

16.1 How Supplied

UBRELVY 50 mg is supplied as white to off-white, capsule-shaped, biconvex tablets debossed with “U50” on one side in unit-dose packets (each packet contains 1 tablet):

- Box of 10 Packets, NDC: 0023-6498-10
- Box of 16 Packets, NDC: 0023-6498-16
- Box of 30 Packets, NDC: 0023-6498-30

UBRELVY 100 mg is supplied as white to off-white capsule-shaped, biconvex tablets debossed with “U100” on one side in unit-dose packets (each packet contains 1 tablet):

- Box of 10 Packets, NDC: 0023-6501-10
- Box of 16 Packets, NDC: 0023-6501-16
- Box of 30 Packets, NDC: 0023-6501-30

16.2 Storage and Handling

Store between 20°C and 25°C (68°F and 77°F): excursions permitted between 15°C and 30°C (59°F and 86°F) [see USP Controlled Room Temperature].

17 PATIENT COUNSELING INFORMATION

Advise the patient to read the FDA-approved patient labeling (Patient Information).

Hypersensitivity Reactions

Inform patients about the signs and symptoms of hypersensitivity reactions and that these reactions can occur with UBRELVY. Advise patients to discontinue UBRELVY and seek immediate medical attention if they experience any symptoms of serious hypersensitivity reactions [see Warnings and Precautions (5.1)].

Hypertension

Inform patients that hypertension can develop or pre-existing hypertension can worsen with UBRELVY, and that they should contact their healthcare providers if they experience elevation in their blood pressure [see Warnings and Precautions (5.2)].

Raynaud’s Phenomenon

Inform patients that Raynaud’s phenomenon can develop or worsen with UBRELVY. Advise patients to discontinue UBRELVY and contact their healthcare provider if they experience signs or symptoms of Raynaud’s phenomenon [see Warnings and Precautions (5.3)].

Drug Interactions

Inform patients that UBRELVY may interact with certain other drugs; therefore, advise patients to report to their healthcare provider the use of any other prescription medications, over-the-counter medications, or herbal products [see Contraindications (4) and Drug Interactions (7.1, 7.2, 7.3)]. Advise patients to inform their healthcare provider of grapefruit juice intake because a dosage modification is recommended with co-administration.

Pregnancy

Advise patients to notify their healthcare provider if they become pregnant during treatment or plan to become pregnant. Encourage pregnant patients to enroll in the registry that monitors pregnancy outcomes in women exposed to UBRELVY during pregnancy [see Use in Specific Populations (8.1)].

Lactation

Inform patients to notify their healthcare provider if they are breastfeeding or plan to breastfeed [see Use in Specific Populations (8.2)].

Manufactured for:

AbbVie Inc.
North Chicago, IL 60064

© 2025 AbbVie. All rights reserved.
UBRELVY and its design are trademarks of Allergan Pharmaceuticals International Limited, an AbbVie company.

20093630 June 2025

Patient Information
UBRELVY® (you-brel-vee)
(ubrogepant)
tablets, for oral use

What is UBRELVY?
UBRELVY is a prescription medicine used for the acute treatment of migraine attacks with or without aura in adults.
UBRELVY is not used to prevent migraine headaches.
It is not known if UBRELVY is safe and effective in children.

Who should not use UBRELVY?
Do not take UBRELVY if you are

- taking medicines known as a strong CYP3A4 inhibitor, such as ketoconazole, clarithromycin, or itraconazole. Ask your healthcare provider if you are not sure if you are taking any of these medicines. Your healthcare provider can tell you if it is safe to take UBRELVY with other medicines.
- allergic to ubrogepant or any of the ingredients in UBRELVY. See the end of this Medication Guide for a complete list of ingredients in UBRELVY.

Before you take UBRELVY tell your healthcare provider about all of your medical conditions, including if you:

- have high blood pressure
- have circulation problems in your fingers and toes
- have liver problems
- have kidney problems
- are pregnant or plan to become pregnant. It is not known if UBRELVY will harm your unborn baby.
  - Pregnancy Registry: There is a pregnancy registry for women who take UBRELVY. The purpose of this registry is to collect information about the health of you and your baby. Talk to your healthcare provider or call 1-833-277-0206 to enroll in this registry. You can also visit http://empresspregnancyregistry.com.
- are breastfeeding or plan to breastfeed. Very small amounts of UBRELVY pass into breast milk. Talk with your healthcare provider if you plan to breastfeed.

Tell your healthcare provider about all the medicines you take, including prescription and over-the-counter medicines, vitamins, and herbal supplements.
Especially tell your healthcare provider if you take any of the following, as your healthcare provider may need to change the dose of UBRELVY:

- verapamil

- cyclosporine

- ciprofloxacin

- fluconazole

- fluvoxamine

- phenytoin

- barbiturates

- rifampin

- St. John’s Wort

- Quinidine

- carvedilol

- eltrombopag

- curcumin

These are not all of the medicines that could affect how UBRELVY works. Your healthcare provider can tell you if it is safe to take UBRELVY with other medicines.
Keep a list of medicines you take to show to your healthcare provider or pharmacist when you get a new medicine.

How should I take UBRELVY?

- Take UBRELVY exactly as your healthcare provider tells you to take it.
- Take UBRELVY with or without food.
- Most patients can take a second tablet 2 hours after the first tablet, as needed.
- You should not take a second tablet within 24 hours if you consume grapefruit or grapefruit juice or are taking medications that may include:

- verapamil

- cyclosporine

- ciprofloxacin

- fluconazole

- fluvoxamine

- It is not known if it is safe to take UBRELVY for more than 8 migraine headaches in 30 days.
- You should write down when you have headaches and when you take UBRELVY so you can talk to your healthcare provider about how UBRELVY is working for you.
- If you take too much UBRELVY, call your healthcare provider or go to the nearest hospital emergency room right away.

What are the possible side effects of UBRELVY?
UBRELVY may cause serious side effects, including:

- Allergic reactions. Allergic reactions can happen after you take UBRELVY. Most reactions happened within hours and were not serious. Some reactions may occur days after taking UBRELVY. Call your healthcare provider or get emergency help right away if you have any of the following symptoms, which may be part of an allergic reaction:
  ○ Swelling of the face, mouth, tongue, or throat
  ○ Trouble breathing
- High blood pressure: High blood pressure or worsening of high blood pressure can happen after you take UBRELVY. Contact your healthcare provider if you have an increase in blood pressure
- Raynaud’s phenomenon: A type of circulation problem can worsen or happen after you take UBRELVY. Raynaud’s phenomenon can lead to your fingers or toes feeling numb, cool, or painful, or changing color from pale, to blue, to red. Contact your healthcare provider if these symptoms occur.

The most common side effects of UBRELVY are nausea and sleepiness.
These are not all of the possible side effects of UBRELVY. Call your healthcare provider for medical advice about side effects. You may report side effects to FDA at 1-800-FDA-1088.

How should I store UBRELVY?

- Store UBRELVY at room temperature between 68ºF to 77ºF (20ºC to 25ºC).

Keep UBRELVY and all medicines out of the reach of children.

General information about the safe and effective use of UBRELVY.
Medicines are sometimes prescribed for purposes other than those listed in a Patient Information leaflet. Do not use UBRELVY for a condition for which it was not prescribed. Do not give UBRELVY to other people, even if they have the same symptoms you have. It may harm them. You can ask your pharmacist or healthcare provider for information about UBRELVY that is written for health professionals.

What are the ingredients in UBRELVY?
Active ingredient: ubrogepant
Inactive ingredients: colloidal silicon dioxide, croscarmellose sodium, mannitol, microcrystalline cellulose, polyvinylpyrrolidone vinyl acetate copolymer, sodium chloride, sodium stearyl fumarate, and vitamin E polyethylene glycol succinate.
Manufactured for:
AbbVie Inc.
North Chicago, IL 60064
© 2025 AbbVie. All rights reserved.
UBRELVY and its design are trademarks of Allergan Pharmaceuticals International Limited, an AbbVie company.

This Patient Package Insert has been approved by the U.S. Food and Drug Administration Issued: 6/2025

20093630

PRINCIPAL DISPLAY PANEL

NDC 0023-6498-10
contains
10 tablets
Rx Only
UBRELVY®
(ubrogepant) tablets
50 mg

PRINCIPAL DISPLAY PANEL

NDC 0023-6501-10
contains
10 tablets
Rx Only
UBRELVY®
(ubrogepant) tablets
100 mg